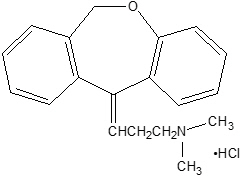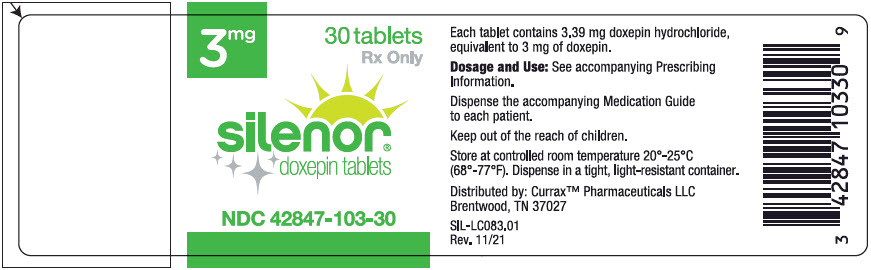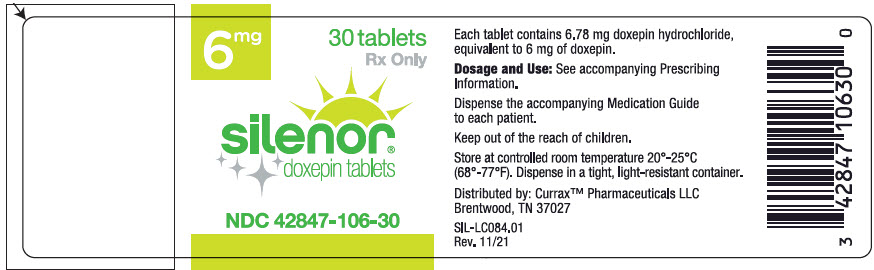 DRUG LABEL: Silenor
NDC: 42847-103 | Form: TABLET
Manufacturer: Currax Pharmaceuticals LLC
Category: prescription | Type: HUMAN PRESCRIPTION DRUG LABEL
Date: 20230508

ACTIVE INGREDIENTS: doxepin hydrochloride 3 mg/1 1
INACTIVE INGREDIENTS: Microcrystalline Cellulose; silicon dioxide; magnesium stearate; FD&C Blue No. 1

HIGHLIGHTS OF PRESCRIBING INFORMATION

These highlights do not include all the information needed to use SILENOR safely and effectively. See full prescribing information for SILENOR.
SILENOR® (doxepin) tablets for oral use
Initial U.S. Approval: 1969

1. INDICATIONS AND USAGE

SILENOR (doxepin) tablets are indicated for the treatment of insomnia characterized by difficulties with sleep maintenance. (1, 14)

2. DOSAGE AND ADMINISTRATION

- Initial dose: 6 mg, once daily for adults (2.1) and 3 mg, once daily for the elderly. (2.1, 2.2)
- Take within 30 minutes of bedtime. Total daily dose should not exceed 6 mg. (2.3)
- Should not be taken within 3 hours of a meal. (2.3, 12.3)

3. DOSAGE FORMS AND STRENGTHS

- 3 mg and 6 mg tablets. Tablets not scored. (3)

4. CONTRAINDICATIONS

- Hypersensitivity to doxepin hydrochloride, inactive ingredients, or other dibenzoxepines. (4.1)
- Co-administration with Monoamine Oxidase Inhibitors (MAOIs): Do not administer if patient is taking MAOIs or has used MAOIs within the past two weeks. (4.2)
- Untreated narrow angle glaucoma or severe urinary retention. (4.3)

5. WARNINGS AND PRECAUTIONS

- Need to Evaluate for Co-morbid Diagnoses: Reevaluate if insomnia persists after 7 to 10 days of use. (5.1)
- Abnormal thinking, behavioral changes, complex behaviors: May include "Sleep-driving" and hallucinations. Immediately evaluate any new onset behavioral changes. (5.2)
- Depression: Worsening of depression or suicidal thinking may occur. Prescribe the least amount feasible to avoid intentional overdose. (5.3)
- CNS-depressant effects: Use can impair alertness and motor coordination. Avoid engaging in hazardous activities such as operating a motor vehicle or heavy machinery after taking drug. (5.4) Do not use with alcohol. (5.4, 7.3)
- Potential additive effects when used in combination with CNS depressants or sedating antihistamines. Dose reduction may be needed. (5.4, 7.4)
- Patients with severe sleep apnea: SILENOR is ordinarily not recommended for use in this population. (8.7)

6. ADVERSE REACTIONS

The most common treatment-emergent adverse reactions, reported in ≥ 2% of patients treated with SILENOR, and more commonly than in patients treated with placebo, were somnolence/sedation, nausea, and upper respiratory tract infection. (6.1)

To report SUSPECTED ADVERSE REACTIONS, contact Currax Pharmaceuticals LLC at 1-800-793-2145 and or FDA at 1-800-FDA-1088 or www.fda.gov/medwatch.

7. DRUG INTERACTIONS

- MAO inhibitors: SILENOR should not be administered in patients on MAOIs within the past two weeks. (4.2)
- Cimetidine: Increases exposure to doxepin. (7.2)
- Alcohol: Sedative effects may be increased with doxepin. (7.3, 5.4)
- CNS Depressants and Sedating Antihistamines: Sedative effects may be increased with doxepin. (7.4, 5.4)
- Tolazamide: A case of severe hypoglycemia has been reported. (7.5)

8. USE IN SPECIFIC POPULATIONS

- Pregnancy: Third trimester use may increase the risk for symptoms of poor adaptation (respiratory distress, temperature instability, feeding difficulties, hypotonia, tremor, irritability) in the neonate. (8.1)
- Lactation: Breastfeeding not recommended. (8.2)
- Pediatric Use: Safety and effectiveness have not been evaluated. (8.4)
- Geriatric Use: The recommended starting dose is 3 mg. Monitor prior to considering dose escalation. (2.2, 8.5)
- Use in Patients with Comorbid Illness: Initiate treatment with 3 mg in patients with hepatic impairment or tendency to urinary retention. (8.6, 4.3)

FULL PRESCRIBING INFORMATION

1. INDICATIONS AND USAGE

SILENOR is indicated for the treatment of insomnia characterized by difficulty with sleep maintenance. The clinical trials performed in support of efficacy were up to 3 months in duration .

2. DOSAGE AND ADMINISTRATION

The dose of SILENOR should be individualized.

2.1. Dosing in Adults

The recommended dose of SILENOR for adults is 6 mg once daily. A 3 mg once daily dose may be appropriate for some patients, if clinically indicated.

2.2. Dosing in the Elderly

The recommended starting dose of SILENOR in elderly patients (≥ 65 years old) is 3 mg once daily. The daily dose can be increased to 6 mg, if clinically indicated.

2.3. Administration

SILENOR should be taken within 30 minutes of bedtime.

To minimize the potential for next day effects, SILENOR should not be taken within 3 hours of a meal [see Clinical Pharmacology (12.3)].

The total SILENOR dose should not exceed 6 mg per day.

3. DOSAGE FORMS AND STRENGTHS

SILENOR is an immediate-release, oval-shaped, tablet for oral administration available in strengths of 3 mg and 6 mg. The tablets are blue (3 mg) or green (6 mg) and are debossed with 3 or 6, respectively, on one side and SP on the other. SILENOR tablets are not scored.

4. CONTRAINDICATIONS

4.1. Hypersensitivity

SILENOR is contraindicated in individuals who have shown hypersensitivity to doxepin HCl, any of its inactive ingredients, or other dibenzoxepines.

4.2. Co-administration with Monoamine Oxidase Inhibitors (MAOIs)

Serious side effects and even death have been reported following the concomitant use of certain drugs with MAO inhibitors. Do not administer SILENOR if patient is currently on MAOIs or has used MAOIs within the past two weeks. The exact length of time may vary depending on the particular MAOI dosage and duration of treatment.

4.3. Glaucoma and Urinary Retention

SILENOR is contraindicated in individuals with untreated narrow angle glaucoma or severe urinary retention.

5. WARNINGS AND PRECAUTIONS

5.1. Need to Evaluate for Comorbid Diagnoses

Because sleep disturbances may be the presenting manifestation of a physical and/or psychiatric disorder, symptomatic treatment of insomnia should be initiated only after careful evaluation of the patient. The failure of insomnia to remit after 7 to 10 days of treatment may indicate the presence of a primary psychiatric and/or medical illness that should be evaluated. Exacerbation of insomnia or the emergence of new cognitive or behavioral abnormalities may be the consequence of an unrecognized psychiatric or physical disorder. Such findings have emerged during the course of treatment with hypnotic drugs.

5.2. Abnormal Thinking and Behavioral Changes

Complex behaviors such as "sleep-driving" (i.e., driving while not fully awake after ingestion of a hypnotic, with amnesia for the event) have been reported with hypnotics. These events can occur in hypnotic-naive as well as in hypnotic-experienced persons. Although behaviors such as "sleep-driving" may occur with hypnotics alone at therapeutic doses, the use of alcohol and other CNS depressants with hypnotics appears to increase the risk of such behaviors, as does the use of hypnotics at doses exceeding the maximum recommended dose. Due to the risk to the patient and the community, discontinuation of SILENOR should be strongly considered for patients who report a "sleep-driving" episode. Other complex behaviors (e.g., preparing and eating food, making phone calls, or having sex) have been reported in patients who are not fully awake after taking a hypnotic. As with "sleep-driving", patients usually do not remember these events. Amnesia, anxiety and other neuro-psychiatric symptoms may occur unpredictably.

5.3. Suicide Risk and Worsening of Depression

In primarily depressed patients, worsening of depression, including suicidal thoughts and actions (including completed suicides), has been reported in association with the use of hypnotics.

Doxepin, the active ingredient in SILENOR, is an antidepressant at doses 10- to 100-fold higher than in SILENOR. Antidepressants increased the risk compared to placebo of suicidal thinking and behavior (suicidality) in children, adolescents, and young adults in short-term studies of major depressive disorder (MDD) and other psychiatric disorders. Risk from the lower dose of doxepin in SILENOR can not be excluded.

It can rarely be determined with certainty whether a particular instance of the abnormal behaviors listed above is drug induced, spontaneous in origin, or a result of an underlying psychiatric or physical disorder. Nonetheless, the emergence of any new behavioral sign or symptom of concern requires careful and immediate evaluation.

5.4. CNS Depressant Effects

After taking SILENOR, patients should confine their activities to those necessary to prepare for bed. Patients should avoid engaging in hazardous activities, such as operating a motor vehicle or heavy machinery, at night after taking SILENOR, and should be cautioned about potential impairment in the performance of such activities that may occur the day following ingestion.

When taken with SILENOR, the sedative effects of alcoholic beverages, sedating antihistamines, and other CNS depressants may be potentiated [see Warnings and Precautions (5.2) and Drug Interactions (7.3, 7.4)]. Patients should not consume alcohol with SILENOR [see Warnings and Precautions (5.2) and Drug Interactions (7.3)]. Patients should be cautioned about potential additive effects of SILENOR used in combination with CNS depressants or sedating antihistamines [see Warnings and Precautions (5.2) and Drug Interactions (7.4)].

6. ADVERSE REACTIONS

The following serious adverse reactions are discussed in greater detail in other sections of labeling:

- Abnormal thinking and behavioral changes [see Warnings and Precautions (5.2)].
- Suicide risk and worsening of depression [see Warnings and Precautions (5.3)].
- CNS Depressant effects [see Warnings and Precautions (5.4)].

6.1. Clinical Trials Experience

The pre-marketing development program for SILENOR included doxepin HCl exposures in 1017 subjects (580 insomnia patients and 437 healthy subjects) from 12 studies conducted in the United States. 863 of these subjects (580 insomnia patients and 283 healthy subjects) participated in six randomized, placebo-controlled efficacy studies with SILENOR doses of 1 mg, 3 mg, and 6 mg for up to 3-months in duration.

Because clinical studies are conducted under widely varying conditions, adverse reaction rates observed in the clinical trials of a drug cannot be directly compared to rates in the clinical trials of another drug and may not reflect the rates observed in practice. However, data from the SILENOR studies provide the physician with a basis for estimating the relative contributions of drug and non-drug factors to adverse reaction incidence rates in the populations studied.

Associated with Discontinuation of Treatment

The percentage of subjects discontinuing Phase 1, 2, and 3 trials for an adverse reaction was 0.6% in the placebo group compared to 0.4%, 1.0%, and 0.7% in the SILENOR 1 mg, 3 mg, and 6 mg groups, respectively. No reaction that resulted in discontinuation occurred at a rate greater than 0.5%.

Adverse Reactions Observed at an Incidence of ≥ 2% in Controlled Trials

Table 1 shows the incidence of treatment-emergent adverse reactions from three long-term (28 to 85 days) placebo-controlled studies of SILENOR in adult (N=221) and elderly (N=494) subjects with chronic insomnia.

Reactions reported by Investigators were classified using a modified MedDRA dictionary of preferred terms for purposes of establishing incidence. The table includes only reactions that occurred in 2% or more of subjects who received SILENOR 3 mg or 6 mg in which the incidence in subjects treated with SILENOR was greater than the incidence in placebo-treated subjects.

Table 1 Incidence (%) of Treatment-Emergent Adverse Reactions in Long-term Placebo-Controlled Clinical Trials
System Organ Class Preferred Term [Includes reactions that occurred at a rate of ≥ 2% in any SILENOR-treated group and at a higher rate than placebo.] | Placebo (N=278) | SILENOR 3 mg (N=157) | SILENOR 6 mg (N=203)
Nervous System Disorders
Somnolence/Sedation | 4 | 6 | 9
Infections and Infestations
Upper Respiratory Tract Infection/Nasopharyngitis | 2 | 4 | 2
Gastroenteritis | 0 | 2 | 0
Gastrointestinal Disorders
Nausea | 1 | 2 | 2
Vascular Disorders
Hypertension | 0 | 3 | < 1

The most common treatment-emergent adverse reaction in the placebo and each of the SILENOR dose groups was somnolence/sedation.

6.2. Studies Pertinent to Safety Concerns for Sleep-promoting Drugs

Residual Pharmacological Effect in Insomnia Trials

Five randomized, placebo-controlled studies in adults and the elderly assessed next-day psychomotor function within 1 hour of awakening utilizing the digit-symbol substitution test (DSST), symbol copying test (SCT), and visual analog scale (VAS) for sleepiness, following night time administration of SILENOR.

In a one-night, double-blind study conducted in 565 healthy adult subjects experiencing transient insomnia, SILENOR 6 mg showed modest negative changes in SCT and VAS.

In a 35-day, double-blind, placebo-controlled, parallel group study of SILENOR 3 and 6 mg in 221 adults with chronic insomnia, small decreases in the DSST and SCT occurred in the 6 mg group.

In a 3-month, double-blind, placebo-controlled, parallel group study in 240 elderly subjects with chronic insomnia, SILENOR 1 mg and 3 mg was comparable to placebo on DSST, SCT, and VAS.

6.3. Other Reactions Observed During the Pre-marketing Evaluation of SILENOR

SILENOR was administered to 1017 subjects in clinical trials in the United States. Treatment-emergent adverse reactions recorded by clinical investigators were standardized using a modified MedDRA dictionary of preferred terms. The following is a list of MedDRA terms that reflect treatment-emergent adverse reactions reported by subjects treated with SILENOR.

Adverse reactions are further categorized by body system and listed in order of decreasing frequency according to the following definitions: Frequent adverse reactions are those that occurred on one or more occasions in at least 1/100 subjects; Infrequent adverse reactions are those that occurred in fewer than 1/100 subjects and more than 1/1000 subjects. Rare adverse reactions are those that occurred in fewer than 1/1000 subjects. Adverse reactions that are listed in Table 1 are not included in the following listing of frequent, infrequent, and rare AEs.

Blood and Lymphatic System Disorders: Infrequent: anemia; Rare: thrombocythemia.

Cardiac Disorders: Rare: atrioventricular block, palpitations, tachycardia, ventricular extrasystoles.

Ear and Labyrinth Disorders: Rare: ear pain, hypoacusis, motion sickness, tinnitus, tympanic membrane perforation.

Eye Disorders: Infrequent: eye redness, vision blurred; Rare: blepharospasm, diplopia, eye pain, lacrimation decreased.

Gastrointestinal Disorders: Infrequent: abdominal pain, dry mouth, gastroesophageal reflux disease, vomiting; Rare: dyspepsia, constipation, gingival recession, haematochezia, lip blister.

General Disorders and Administration Site Conditions: Infrequent: asthenia, chest pain, fatigue; Rare: chills, gait abnormal, edema peripheral.

Hepatobiliary Disorders: Rare: hyperbilirubinemia.

Immune System Disorders: Rare: hypersensitivity.

Infections and Infestations: Infrequent: bronchitis, fungal infection, laryngitis, sinusitis, tooth infection, urinary tract infection, viral infection; Rare: cellulitis staphylococcal, eye infection, folliculitis, gastroenteritis viral, herpes zoster, infective tenosynovitis, influenza, lower respiratory tract infection, onychomycosis, pharyngitis, pneumonia.

Injury, Poisoning and Procedural Complications: Infrequent: back injury, fall, joint sprain; Rare: bone fracture, skin laceration.

Investigations: Infrequent: blood glucose increased; Rare: alanine aminotransferase increased, blood pressure decreased, blood pressure increased, electrocardiogram ST-T segment abnormal, electrocardiogram QRS complex abnormal, heart rate decreased, neutrophil count decreased, QRS axis abnormal, transaminases increased.

Metabolism and Nutrition Disorders: Infrequent: anorexia, decreased appetite, hyperkalemia, hypermagnesemia, increased appetite; Rare: hypokalemia.

Musculoskeletal and Connective Tissue Disorders: Infrequent: arthralgia, back pain, myalgia, neck pain, pain in extremity; Rare: joint range of motion decreased, muscle cramp, sensation of heaviness.

Neoplasms Benign, Malignant and Unspecified (Including Cysts and Polyps): Rare: lung adenocarcinoma stage I, malignant melanoma.

Nervous System Disorders: Frequent: dizziness; Infrequent: dysgeusia, lethargy, parasthesia, syncope; Rare: ageusia, ataxia, cerebrovascular accident, disturbance in attention, migraine, sleep paralysis, syncope vasovagal, tremor.

Psychiatric Disorders: Infrequent: abnormal dreams, adjustment disorder, anxiety, depression; Rare: confusional state, elevated mood, insomnia, libido decreased, nightmare.

Reproductive System and Breast Disorders: Rare: breast cyst, dysmenorrhea.

Renal and Urinary Disorders: Rare: dysuria, enuresis, hemoglobinuria, nocturia.

Respiratory, Thoracic and Mediastinal Disorders: Infrequent: nasal congestion, pharyngolaryngeal pain, sinus congestion, wheezing; Rare: cough, crackles lung, nasopharyngeal disorder, rhinorrhea, dyspnea.

Skin and Subcutaneous Tissue Disorders: Infrequent: skin irritation; Rare: cold sweat, dermatitis, erythema, hyperhidrosis, pruritis, rash, rosacea.

Surgical and Medical Procedures: Rare: arthrodesis.

Vascular Disorders: Infrequent: pallor; Rare: blood pressure inadequately controlled, hematoma, hot flush.

In addition, the reactions below have been reported for other tricyclics and may be idiosyncratic (not related to dose).

Allergic: photosensitization, skin rash.

Hematologic: agranulocytosis, eosinophilia, leukopenia, purpura, thrombocytopenia.

7. DRUG INTERACTIONS

7.1. Cytochrome P450 Isozymes

SILENOR is primarily metabolized by hepatic cytochrome P450 isozymes CYP2C19 and CYP2D6, and to a lesser extent, by CYP1A2 and CYP2C9. Inhibitors of these isozymes may increase the exposure of doxepin. SILENOR is not an inhibitor of any CYP isozymes at therapeutically relevant concentrations. The ability of SILENOR to induce CYP isozymes is not known.

7.2. Cimetidine

SILENOR exposure is doubled with concomitant administration of cimetidine, a nonspecific inhibitor of CYP isozymes. A maximum dose of 3 mg is recommended in adults and elderly when cimetidine is co-administered with SILENOR [see Clinical Pharmacology (12.3)]

7.3. Alcohol

When taken with SILENOR, the sedative effects of alcohol may be potentiated [see Warnings and Precautions (5.2, 5.4)].

7.4. CNS Depressants and Sedating Antihistamines

When taken with SILENOR, the sedative effects of sedating antihistamines and CNS depressants may be potentiated [see Warnings and Precautions (5.2, 5.4)].

7.5. Tolazamide

A case of severe hypoglycemia has been reported in a type II diabetic patient maintained on tolazamide (1 g/day) 11 days after the addition of oral doxepin (75 mg/day).

8. USE IN SPECIFIC POPULATIONS

8.1. Pregnancy

Risk Summary

Available data from published epidemiologic studies and postmarketing reports have not established an increased risk of major birth defects or miscarriage (see Data). There are risks of poor neonatal adaptation with exposure to tricyclic antidepressants (TCAs), including doxepin, during pregnancy (see Clinical Considerations). In animal reproduction studies, oral administration of doxepin to rats and rabbits during the period of organogenesis caused adverse developmental effects at doses 65 and 23 times the maximum recommended human dose (MRHD) of 6 mg/day based on AUC, respectively. Oral administration of doxepin to pregnant rats during pregnancy and lactation resulted in decreased pup survival and a delay in pup growth at doses 60 times the MRHD based on AUC (see Data).

The estimated background risk of major birth defects and miscarriage for the indicated population is unknown. All pregnancies have a background risk of major birth defect, loss, or other adverse outcomes. In the U.S. general population, the estimated background risk of major birth defects and miscarriage in clinically recognized pregnancies is 2 to 4% and 15 to 20%, respectively.

Clinical Considerations

Fetal/Neonatal adverse reactions

Neonates exposed to TCAs, including doxepin, late in the third trimester have developed complications requiring prolonged hospitalization, respiratory support, and tube feeding. Such complications can arise immediately upon delivery. Reported clinical findings have included respiratory distress, cyanosis, apnea, seizures, temperature instability, feeding difficulty, vomiting, hypoglycemia, hypotonia, hyperreflexia, tremor, jitteriness, irritability and constant crying. These findings are consistent with either direct toxic effects of TCAs or possibly a drug discontinuation syndrome. Monitor neonates who were exposed to SILENOR in the third trimester of pregnancy for poor neonatal adaptation syndrome.

Data

Human Data

Published epidemiologic studies of pregnant women exposed to TCAs, including doxepin, have not established an association with major birth defects, miscarriage or adverse maternal outcomes. Methodological limitations of these observational studies include small sample size and lack of adequate controls.

Animal Data

When doxepin (30, 100, and 150 mg/kg/day) was administered orally to pregnant rats during the period of organogenesis, developmental toxicity (increased incidences of fetal structural abnormalities consisting of non-ossified bones in the skull and sternum and decreased fetal body weights) and maternal toxicity were noted at ≥100 mg/kg/day, which produced plasma exposures (AUCs) of doxepin and nordoxepin (the primary metabolite in humans) approximately 65 and 53 times, respectively, the plasma AUCs at the MRHD. The plasma exposures at the no-effect dose for embryo-fetal developmental toxicity in rats (30 mg/kg/day) are approximately 6 and 5 times the plasma AUCs for doxepin and nordoxepin, respectively, at the MRHD. When doxepin (10, 30, and 60 mg/kg/day) was administered orally to pregnant rabbits during the period of organogenesis, fetal body weights were reduced at the highest dose in the absence of maternal toxicity, which produced plasma AUCs of doxepin and nordoxepin approximately 23 and 56 times, respectively, the plasma AUCs at the MRHD. The plasma exposures at the no-effect dose for developmental effects (30 mg/kg/day) are approximately 8 and 25 times the plasma AUCs for doxepin and nordoxepin, respectively, at the MRHD. Oral administration of doxepin (10, 30, and 100 mg/kg/day) to rats throughout pregnancy and lactation resulted in decreased pup survival and transient growth delay at the highest dose, which produced plasma AUCs of doxepin and nordoxepin approximately 60 and 39 times, respectively, the plasma AUCs at the MRHD. The plasma exposures at the no-effect dose for adverse effects on pre- and postnatal development in rats (30 mg/kg/day) are approximately 2 and 1 times the plasma AUCs for doxepin and nordoxepin, respectively, at the MRHD.

8.2. Lactation

Risk Summary

Data from the published literature report the presence of doxepin and nordoxepin in human milk. There are reports of excess sedation, respiratory depression, poor sucking and swallowing, and hypotonia in breastfed infants exposed to doxepin. There are no data on the effects of doxepin on milk production. Because of the potential for serious adverse reactions, including excess sedation and respiratory depression in a breastfed infant, clinicians should advise patients that breastfeeding is not recommended during treatment with SILENOR.

Clinical Considerations

Infants exposed to SILENOR through breast milk should be monitored for excess sedation, respiratory depression and hypotonia.

8.3. Females and Males of Reproductive Potential

Infertility

Based on results from animal fertility studies conducted in rats, doxepin may reduce fertility in females and males of reproductive potential [see Nonclinical Toxicology (13.1)]. It is unknown if the effects are reversible.

8.4. Pediatric Use

The safety and effectiveness of SILENOR in pediatric patients have not been evaluated.

8.5. Geriatric Use

A total of 362 subjects who were ≥ 65 years and 86 subjects who were ≥ 75 years received SILENOR in controlled clinical studies. No overall differences in safety or effectiveness were observed between these subjects and younger adult subjects. Greater sensitivity of some older individuals cannot be ruled out.

Sleep-promoting drugs may cause confusion and over-sedation in the elderly. A starting dose of 3 mg is recommended in this population and evaluation prior to considering dose escalation is recommended [see Dosage and Administration (2.2)].

8.6. Use in Patients with Hepatic Impairment

Patients with hepatic impairment may display higher doxepin concentrations than healthy individuals. Initiate SILENOR treatment with 3 mg in patients with hepatic impairment and monitor closely for adverse daytime effects. [see Clinical Pharmacology (12.3)]

8.7. Use in Patients with Sleep Apnea

SILENOR has not been studied in patients with obstructive sleep apnea. Since hypnotics have the capacity to depress respiratory drive, precautions should be taken if SILENOR is prescribed to patients with compromised respiratory function. In patients with severe sleep apnea, SILENOR is ordinarily not recommended for use.

9. DRUG ABUSE AND DEPENDENCE

9.1. Controlled Substance

Doxepin is not a controlled substance.

9.2. Abuse

Doxepin is not associated with abuse potential in animals or in humans. Physicians should carefully evaluate patients for history of drug abuse and follow such patients closely, observing them for signs of misuse or abuse of doxepin (e.g., incrementation of dose, drug-seeking behavior).

9.3. Dependence

In a brief assessment of adverse events observed during discontinuation of doxepin following chronic administration, no symptoms indicative of a withdrawal syndrome were observed. Thus, doxepin does not appear to produce physical dependence.

10. OVERDOSAGE

Doxepin is routinely administered for indications other than insomnia at doses 10- to 50-fold higher than the highest recommended dose of SILENOR.

The signs and symptoms associated with doxepin use at doses several-fold higher than the maximum recommended dose (Excessive dose) of SILENOR for the treatment of insomnia are described [see Overdosage (10.1)], as are signs and symptoms associated with higher multiples of the maximum recommended dose (Critical overdose) [see Overdosage (10.2)].

10.1. Signs and Symptoms of Excessive Doses

The following adverse effects have been associated with use of doxepin at doses higher than 6 mg.

Anticholinergic Effects: constipation and urinary retention.

Central Nervous System: disorientation, hallucinations, numbness, paresthesias, extrapyramidal symptoms, seizures, tardive dyskinesia.

Cardiovascular: hypotension.

Gastrointestinal: aphthous stomatitis, indigestion.

Endocrine: raised libido, testicular swelling, gynecomastia in males, enlargement of breasts and galactorrhea in the female, raising or lowering of blood sugar levels, and syndrome of inappropriate antidiuretic hormone secretion.

Other: tinnitus, weight gain, sweating, flushing, jaundice, alopecia, exacerbation of asthma, and hyperpyrexia (in association with chlorpromazine).

10.2. Signs and Symptoms of Critical Overdose

Manifestations of doxepin critical overdose include: cardiac dysrhythmias, severe hypotension, convulsions, and CNS depression including coma. Electrocardiogram changes, particularly in QRS axis or width, are clinically significant indicators of tricyclic compound toxicity. Other signs of overdose may include, but are not limited to: confusion, disturbed concentration, transient visual hallucinations, dilated pupils, agitation, hyperactive reflexes, stupor, drowsiness, muscle rigidity, vomiting, hypothermia, hyperpyrexia.

10.3 Recommended Management

As management of overdose is complex and changing, it is recommended that the physician contact a poison control center for current information on treatment. In addition, the possibility of a multiple drug ingestion should be considered.

If an overdose is suspected, an ECG should be obtained and cardiac monitoring should be initiated immediately. The patient's airway should be protected, an intravenous line should be established, and gastric decontamination should be initiated. A minimum of six hours of observation with cardiac monitoring and observation for signs of CNS or respiratory depression, hypotension, cardiac dysrhythmias and/or conduction blocks, and seizures is strongly advised. If signs of toxicity occur at any time during this period, extended monitoring is recommended. There are case reports of patients succumbing to fatal dysrhythmias late after overdose; these patients had clinical evidence of significant poisoning prior to death and most received inadequate gastrointestinal decontamination. Monitoring of plasma drug levels should not guide management of the patient.

Gastrointestinal Decontamination

All patients suspected of overdose should receive gastrointestinal decontamination. This should include large volume gastric lavage followed by administration of activated charcoal. If consciousness is impaired, the airway should be secured prior to lavage. Emesis is contraindicated.

Cardiovascular

A maximal limb-lead QRS duration of ≥0.10 seconds may be the best indication of the severity of an overdose. Serum alkalinization, using intravenous sodium bicarbonate should be used to maintain the serum pH in the range of 7.45 to 7.55 for patients with dysrhythmias and/or QRS widening. If the pH response is inadequate, hyperventilation may also be used. Concomitant use of hyperventilation and sodium bicarbonate should be done with extreme caution, with frequent pH monitoring. A pH >7.60 or a pCO2 <20 mm Hg is undesirable. Dysrhythmias unresponsive to sodium bicarbonate therapy/hyperventilation may respond to lidocaine or phenytoin. Type 1A and 1C antiarrhythmics are generally contraindicated (e.g., quinidine, disopyramide, and procainamide).

In rare instances, hemoperfusion may be beneficial in acute refractory cardiovascular instability in patients with acute toxicity. However, hemodialysis, peritoneal dialysis, exchange transfusions, and forced diuresis generally have been reported as ineffective in treatment of tricyclic compound poisoning.

Central Nervous System

In patients with central nervous system depression, early intubation is advised because of the potential for abrupt deterioration. Seizures should be controlled with benzodiazepines, or, if these are ineffective, other anticonvulsants (e.g., phenobarbital or phenytoin). Physostigmine is not recommended except to treat life-threatening symptoms that have been unresponsive to other therapies, and then only in consultation with a poison control center.

Psychiatric Follow-up

Since overdose often is deliberate, patients may attempt suicide by other means during the recovery phase. Psychiatric referral may be appropriate.

Pediatric Management

The principles of management of child and adult overdoses are similar. It is strongly recommended that the physician contact the local poison control center for specific pediatric treatment.

11. DESCRIPTION

SILENOR (doxepin) is available in 3 mg and 6 mg strength tablets for oral administration. Each tablet contains 3.39 mg or 6.78 mg doxepin hydrochloride, equivalent to 3 mg and 6mg of doxepin, respectively.

Chemically, doxepin hydrochloride is an (E) and (Z) geometric, isomeric mixture of 1 propanamine, 3-dibenz[b,e]oxepin-11(6H)ylidene-N,N-dimethyl-hydrochloride. It has the following structure:

Doxepin hydrochloride is a white crystalline powder, with a slight amine-like odor, that is readily soluble in water. It has a molecular weight of 315.84 and molecular formula of C19 H21 NO∙HCl.

Each SILENOR tablet includes the following inactive ingredients: microcrystalline cellulose, colloidal silicon dioxide, and magnesium stearate. The 3 mg tablet also contains FD&C Blue No.1. The 6 mg tablet also contains D&C Yellow No. 10 and FD&C Blue No. 1.

12. CLINICAL PHARMACOLOGY

12.1. Mechanism of Action

The mechanism of action of doxepin in sleep maintenance is unclear; however, doxepin's effect could be mediated through antagonism of the H1 receptor.

12.2. Pharmacodynamics

Doxepin has high binding affinity to the H1 receptor (Ki < 1 nM).

Cardiac Electrophysiology

In a thorough QTc prolongation clinical study in healthy subjects, doxepin had no effect on QT intervals or other electrocardiographic parameters after multiple daily doses up to 50 mg.

12.3. Pharmacokinetics

Absorption

The median time to peak concentrations (Tmax) of doxepin occurred at 3.5 hours postdose after oral administration of a 6 mg dose to fasted healthy subjects. Peak plasma concentrations (Cmax) of SILENOR increased in approximately a dose-proportional manner for 3 mg and 6 mg doses. The AUC was increased by 41% and Cmax by 15% when 6 mg SILENOR was administered with a high fat meal. Additionally, compared to the fasted state, Tmax was delayed by approximately 3 hours. Therefore, for faster onset and to minimize the potential for next day effects, it is recommended that SILENOR not be taken within 3 hours of a meal [see Dosage and Administration (2.3)].

Distribution

SILENOR is widely distributed throughout the body tissues. The mean apparent volume of distribution following a single 6 mg oral dose of SILENOR to healthy subjects was 11,930 liters. SILENOR is approximately 80% bound to plasma proteins.

Metabolism

Following oral administration, SILENOR is extensively metabolized by oxidation and demethylation. The primary metabolite is N-desmethyldoxepin (nordoxepin).

The primary metabolite undergoes further biotransformation to glucuronide conjugates.

In vitro studies have shown that CYP2C19 and CYP2D6 are the major enzymes involved in doxepin metabolism, and that CYP1A2 and CYP2C9 are involved to a lesser extent.

Doxepin appears not to have inhibitory effects on human CYP enzymes at therapeutic concentrations. The potential of doxepin to induce metabolizing enzymes is not known. Doxepin is not a Pgp substrate.

Excretion

Doxepin is excreted in the urine mainly in the form of glucuronide conjugates.

Less than 3% of a doxepin dose is excreted in the urine as parent compound or nordoxepin. The apparent terminal half-life (t ½) of doxepin was 15.3 hours and for nordoxepin was 31 hours.

Drug Interactions

Since doxepin is metabolized by CYP2C19 and CYP2D6, inhibitors of these CYP isozymes may increase the exposure of doxepin.

Cimetidine

The effect of cimetidine, a non-specific inhibitor of CYP1A2, 2C19, 2D6, and 3A4, on SILENOR plasma concentrations was evaluated in healthy subjects. When cimetidine 300 mg BID was co-administered with a single dose of SILENOR 6 mg, there was approximately a 2-fold increase in SILENOR Cmax and AUC compared to SILENOR given alone. A maximum dose of doxepin in adults and elderly should be 3 mg, when doxepin is co-administered with cimetidine.

Sertraline

The effect of sertraline HCl, a selective serotonin reuptake inhibitor, on doxepin plasma concentrations was evaluated in a daytime study conducted with 24 healthy subjects. Following co-administration of doxepin 6 mg with sertraline 50 mg (at steady-state), the doxepin mean AUC and Cmax estimates were approximately 21% and 32% higher, respectively, than those obtained following administration of doxepin alone. Psychomotor function as measured by the digit symbol substitution test and symbol copy test performance was decreased more at 2-4 hours post dosing for the combination of sertraline and doxepin as compared to doxepin alone, but subjective measures of alertness were comparable for the two treatments.

Special Populations

Renal Impairment

The effects of renal impairment on doxepin pharmacokinetics have not been studied. Because only small amounts of doxepin and nordoxepin are eliminated in the urine, renal impairment would not be expected to result in significantly altered doxepin concentrations.

Hepatic Impairment

The effects of SILENOR in patients with hepatic impairment have not been studied. Because doxepin is extensively metabolized by hepatic enzymes, patients with hepatic impairment may display higher doxepin concentrations than healthy individuals.

Poor Metabolizers of CYPs

Poor metabolizers of CYP2C19 and CYP2D6 may have higher doxepin plasma levels than normal subjects.

13. NONCLINICAL TOXICOLOGY

13.1. Carcinogenesis, Mutagenesis, Impairment of Fertility

Carcinogenesis

No evidence of carcinogenic potential was observed when doxepin was administered orally to hemizygous Tg.rasH2 mice for 26 weeks at doses of 25, 50, 75, and 100 mg/kg/day.

Mutagenesis

Doxepin was negative in in vitro (bacterial reverse mutation, chromosomal aberration in human lymphocytes) and in vivo (rat micronucleus) assays.

Impairment of Fertility

When doxepin (10, 30, and 100 mg/kg/day) was orally administered to male and female rats prior to, during and after mating, adverse effects on fertility (increased copulatory interval and decreased corpora lutea, implantation, viable embryos and litter size) and sperm parameters (increased percentages of abnormal sperm and decreased sperm motility) were observed. The plasma exposures (AUC) for doxepin and nordoxepin at the no-effect dose for adverse effects on reproductive performance and fertility in rats (10 mg/kg/day) are less than those in humans at the maximum recommended human dose of 6 mg/day.

14. CLINICAL STUDIES

14.1. Controlled Clinical Trials

The efficacy of SILENOR for improving sleep maintenance was supported by six randomized, double-blind studies up to 3 months in duration that included 1,423 subjects, 18 to 93 years of age, with chronic (N=858) or transient (N=565) insomnia. SILENOR was evaluated at doses of 1 mg, 3 mg, and 6 mg relative to placebo in inpatient (sleep laboratory) and outpatient settings.

The primary efficacy measures for assessment of sleep maintenance were the objective and subjective time spent awake after sleep onset (respectively, objective Wake After Sleep Onset [WASO] and subjective WASO).

Subjects in studies of chronic insomnia were required to have at least a 3-month history of insomnia.

Chronic Insomnia

Adults

A randomized, double-blind, parallel-group study was conducted in adults (N = 221) with chronic insomnia.

SILENOR 3 mg and 6 mg was compared to placebo out to 30 days.

SILENOR 3 mg and 6 mg were superior to placebo on objective WASO. SILENOR 3 mg was superior to placebo on subjective WASO at night 1 only. SILENOR 6 mg was superior to placebo on subjective WASO at night 1, and nominally superior at some later time points out to Day 30.

Elderly

Elderly subjects with chronic insomnia were assessed in two parallel-group studies.

The first randomized, double-blind study assessed SILENOR 1 mg and 3 mg relative to placebo for 3 months in inpatient and outpatient settings in elderly subjects (N=240) with chronic insomnia. SILENOR 3 mg was superior to placebo on objective WASO.

The second randomized, double-blind study assessed SILENOR 6 mg relative to placebo for 4 weeks in an outpatient setting in elderly subjects (N=254) with chronic insomnia. On subjective WASO, SILENOR 6 mg was superior to placebo.

Transient Insomnia

Healthy adult subjects (N=565) experiencing transient insomnia during the first night in a sleep laboratory were evaluated in a randomized, double-blind, parallel-group, single-dose study of SILENOR 6 mg relative to placebo. SILENOR 6 mg was superior to placebo on objective WASO and subjective WASO.

Withdrawal Effects

Potential withdrawal effects were assessed in a 35-day double blind study of adults with chronic insomnia who were randomized to placebo, SILENOR 3 mg, or SILENOR 6 mg. There was no indication of a withdrawal syndrome after discontinuation of SILENOR treatment (3 mg or 6 mg), as measured by the Tyrer's Symptom Checklist. Discontinuation-period emergent nausea and vomiting occurred in 5% of subjects treated with 6 mg SILENOR, versus 0% in 3 mg and placebo subjects.

Rebound Insomnia Effects

Rebound insomnia, defined as a worsening in WASO compared with baseline following discontinuation of treatment, was assessed in a double-blind, 35-day study in adults with chronic insomnia. SILENOR 3 mg and 6 mg showed no evidence of rebound insomnia.

16. HOW SUPPLIED/STORAGE AND HANDLING

16.1. How Supplied

SILENOR 3 mg tablets are oval shaped, blue, identified with debossed markings of "3" on one side and "SP" on the other, and are supplied as:

NDC 42847-103-30 | Bottle of 30

SILENOR 6 mg tablets are oval shaped, green, identified with debossed markings of "6" on one side and "SP" on the other, and are supplied as:

NDC 42847-106-30 | Bottle of 30

16.2. Storage and Handling

Store at controlled room temperature 20° - 25°C (68° - 77°F), protected from light.

17. PATIENT COUNSELING INFORMATION

Advise the patient to read the FDA-approved patient labeling (Medication Guide).

Sleep-driving and Other Complex Behaviors

There have been reports of people getting out of bed after taking a hypnotic and driving their cars while not fully awake, often with no memory of the event. If a patient experiences such an episode, it should be reported to his or her doctor immediately, since "sleep-driving" can be dangerous. This behavior is more likely to occur when a hypnotic is taken with alcohol or other central nervous system depressants [see Warnings and Precautions (5.2, 5.4) and Drug Interactions (7.3, 7.4)]. Other complex behaviors (e.g., preparing and eating food, making phone calls, or having sex) have been reported in patients who are not fully awake after taking a hypnotic. As with "sleep-driving", patients usually do not remember these events.

In addition, patients should be advised to report all concomitant medications to the prescriber. Patients should be instructed to report events such as "sleep-driving" and other complex behaviors immediately to the prescriber.

Suicide risk and Worsening of Depression

Patients, their families, and their caregivers should be encouraged to be alert to worsening of depression, including suicidal thoughts and actions. Such symptoms should be reported to the patient's prescriber or health professional.

Administration Instructions

Patients should be counseled to take SILENOR within 30 minutes of bedtime and should confine their activities to those necessary to prepare for bed. SILENOR tablets should not be taken with or immediately after a meal [see Dosage and Administration (2.3)]. Advise patients NOT to take SILENOR when drinking alcohol [see Warnings and Precautions (5.2, 5.4) and Drug Interactions (7.3)].

Pregnancy

Advise patients that SILENOR use late in pregnancy may increase the risk for neonatal complications requiring prolonged hospitalization, respiratory support or tube feeding [see Use in Specific Populations (8.1)].

Lactation

Advise patients that breastfeeding is not recommended during treatment with SILENOR [see Use in Specific Populations (8.2)].

Infertility

Inform patients that SILENOR may cause reduced fertility. It is not known whether these effects on fertility are reversible [see Use in Specific Populations (8.3) and Nonclinical Toxicology (13.1)].

Distributed by:
Currax™ Pharmaceuticals LLC
Brentwood, TN 37027 USA

SIL-LC087.02

MEDICATION GUIDE
SILENOR® [si-leh-nor]
(doxepin)
tablets

What is the most important information I should know about SILENOR?

SILENOR can cause serious side effects including:

After taking SILENOR, you may get up out of bed while not being fully awake and do an activity that you do not know you are doing. The next morning, you may not remember that you did anything during the night. You have a higher chance for doing these activities if you drink alcohol or take other medicines that make you sleepy with SILENOR. Reported activities include:

- driving a car ("sleep-driving")
- making and eating food
- talking on the phone
- having sex
- sleep-walking

Stop taking SILENOR and call your healthcare provider right away if you find out that you have done any of the above activities after taking SILENOR.
Important:

- Take SILENOR exactly as prescribed
  - Do not take more SILENOR than prescribed.

Take SILENOR 30 minutes before bedtime. After taking SILENOR, you should only do activities needed to get ready for bed.

What is SILENOR?

SILENOR is a prescription medicine used to treat adults who have trouble staying asleep.

It is not known if SILENOR is safe and effective in children.

Do not take SILENOR if you:

- are allergic to any of the ingredients in SILENOR. See the end of this Medication Guide for a complete list of ingredients in SILENOR.
- take a monoamine oxidase inhibitor (MAOI) medicine or have taken an MAOI in the last 14 days (2 weeks). Ask your healthcare provider if you are not sure if your medicine is an MAOI.
- have an eye problem called narrow angle glaucoma that is not being treated or have trouble urinating that is severe.

Before taking SILENOR, tell your healthcare provider about all of your medical conditions, including if you:

- have a history of depression, mental illness, or suicidal thoughts
- have severe sleep apnea
- have kidney or liver problems
- have a history of drug or alcohol abuse or addiction
- have a history of glaucoma or trouble urinating that is severe
- are pregnant or plan to become pregnant. Taking SILENOR in the third trimester of pregnancy may harm your unborn baby. Talk to your healthcare provider if you are pregnant or plan to become pregnant during treatment with SILENOR.
  - Babies born to mothers who take certain medicines, including SILENOR, during the third trimester of pregnancy may have symptoms of sedation, such as breathing problems, sluggishness, low muscle tone, feeding problems, and withdrawal symptoms.
- are breastfeeding or plan to breastfeed. SILENOR can pass into your breast milk and may harm your baby. You should not breastfeed during treatment with SILENOR. Talk to your healthcare provider about the best way to feed your baby during treatment with SILENOR.

Tell your healthcare provider about all of the medicines you take including prescription and over-the-counter medicines, vitamins and herbal supplements.

SILENOR and other medicines may affect each other causing side effects. SILENOR may affect the way other medicines work, and other medicines may affect how SILENOR works.

Especially tell your healthcare provider if you take:

- certain allergy medicines (antihistamines) or other medicines that can make you sleepy or affect your breathing

Know the medicines you take. Keep a list of your medicines with you to show your healthcare provider and pharmacist each time you get a new medicine.

How should I take SILENOR?

- Take SILENOR exactly as your healthcare provider tells you to take it.
- Your healthcare provider may change your dose if needed.
- Take SILENOR within 30 minutes of bedtime. After taking SILENOR, you should only do activities to get ready for bed.
- Do not take SILENOR within 3 hours of a meal. SILENOR may make you sleepy the next day if taken with or right after a meal.
- Call your healthcare provider if your sleep problems get worse or do not get better within 7 to 10 days. This may mean that there is another condition causing your sleep problem.
- If you take too much SILENOR, call your healthcare provider or get medical help right away.

What should I avoid during treatment with SILENOR?

- You should not drink alcohol or take other medicines that may make you sleepy or dizzy during treatment with SILENOR because it may make your sleepiness or dizziness much worse.
- You should not drive, operate heavy machinery, or do other dangerous activities after taking SILENOR. You may still feel sleepy the next day after taking SILENOR. Do not drive or do other dangerous activities after taking SILENOR until you feel fully awake.

What are the possible side effects of SILENOR?

SILENOR can cause serious side effects including:

- See "What is the most important information I should know about SILENOR?"
- Risk of suicide and worsening of depression. Worsening of depression, including suicidal thoughts and actions can happen during treatment with SILENOR. Call your healthcare provider right away if you have any thoughts of suicide, dying, or worsening depression.

The most common side effects of SILENOR include:

- drowsiness or tiredness

- nausea

- upper respiratory tract infection

SILENOR may cause fertility problems in females and males, which may affect your ability to have children. Talk to your healthcare provider if you have concerns about fertility.

These are not all of the possible side effects of SILENOR. Call your doctor for medical advice about side effects. You may report side effects to FDA at 1-800-FDA-1088.

How should I store SILENOR?

- Store SILENOR at room temperature between 68°to 77° F (20° to 25°C).
- Protect from light.

Keep SILENOR and all medicines out of the reach of children.

General Information about the safe and effective use of SILENOR.

Medicines are sometimes prescribed for purposes other than those listed in a Medication Guide. Do not use SILENOR for a condition for which it was not prescribed. Do not give SILENOR to other people, even if they have the same symptoms that you have. It may harm them. You can ask your pharmacist or healthcare provider for information about SILENOR that is written for healthcare professionals.

What are the ingredients in SILENOR?

Active Ingredient: doxepin hydrochloride

Inactive Ingredients: microcrystalline cellulose, colloidal silicon dioxide, and magnesium stearate. The 3 mg tablet also contains FD&C Blue No. 1. The 6 mg tablet also contains FD&C Yellow No. 10 and FD&C Blue No. 1.

Distributed by: Currax™ Pharmaceuticals LLC, Brentwood, TN 37027 USA
SIL-LC088.02
For more information, contact Currax Pharmaceuticals LLC at 1-800-793-2145.

This Medication Guide has been approved by the U.S. Food and Drug Administration.

Revised: 12/2022

PRINCIPAL DISPLAY PANEL - 3 mg Tablet Bottle Label

3mg

30 tablets
Rx Only

silenor®
doxepin tablets

NDC 42847-103-30

PRINCIPAL DISPLAY PANEL - 6 mg Tablet Bottle Label

6mg

30 tablets
Rx Only

silenor®
doxepin tablets

NDC 42847-106-30